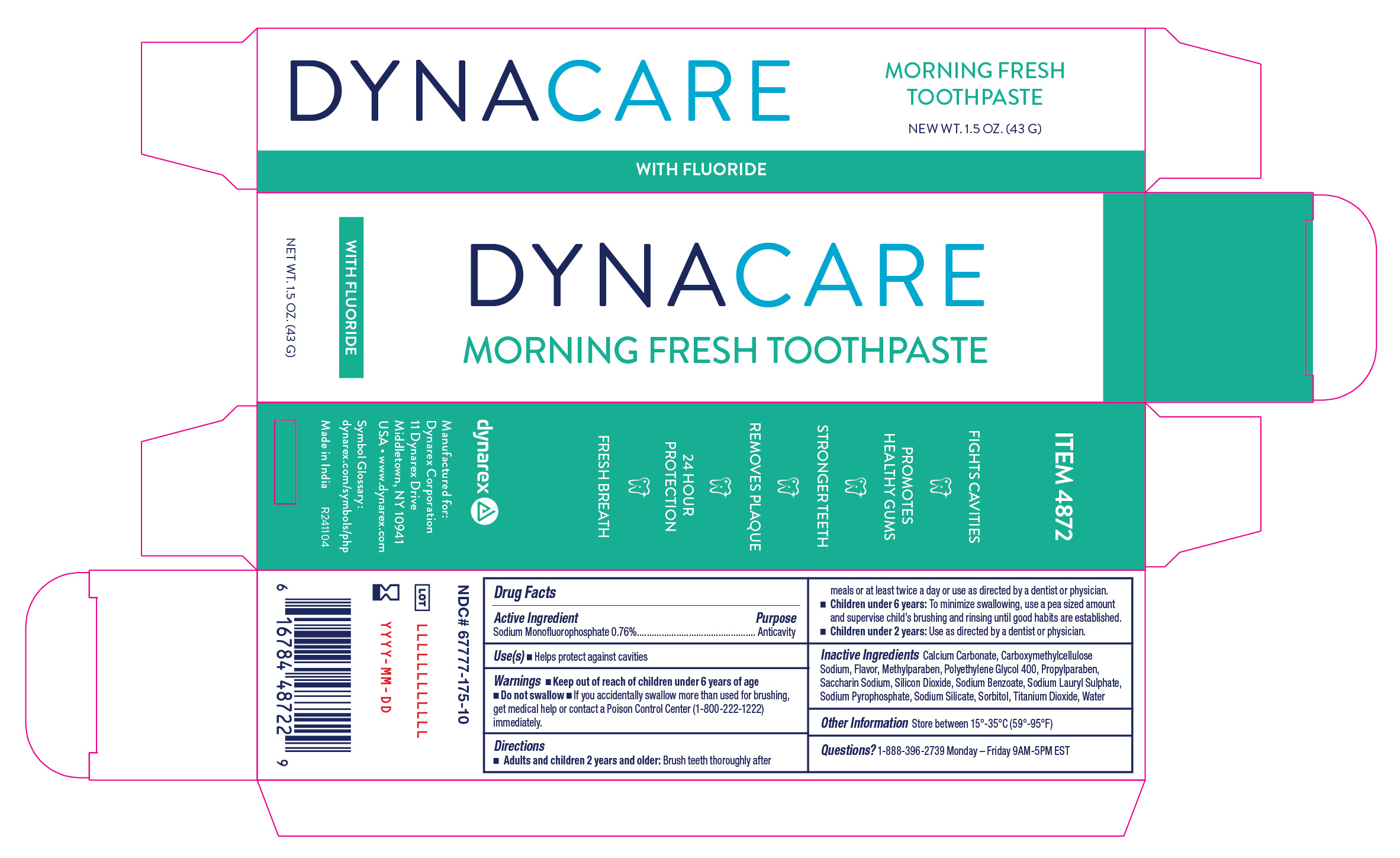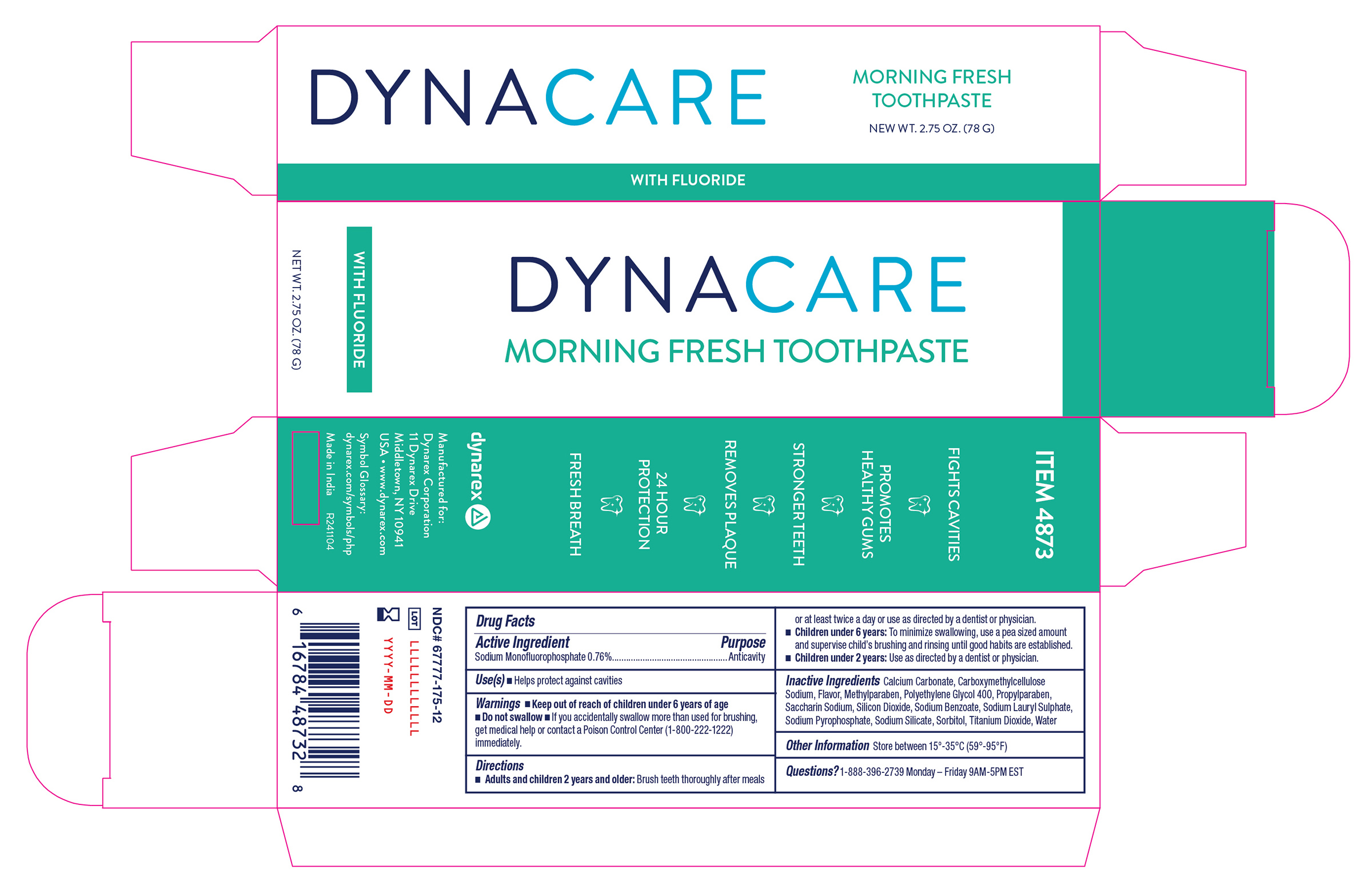 DRUG LABEL: Morning Fresh
NDC: 67777-175 | Form: PASTE
Manufacturer: Dynarex Corporation
Category: otc | Type: HUMAN OTC DRUG LABEL
Date: 20241227

ACTIVE INGREDIENTS: SODIUM MONOFLUOROPHOSPHATE 76 mg/1 g
INACTIVE INGREDIENTS: SODIUM BENZOATE; SORBITOL; SACCHARIN SODIUM; WATER; CARBOXYMETHYLCELLULOSE SODIUM; SODIUM LAURYL SULFATE; SILICON DIOXIDE; SODIUM SILICATE; SODIUM PYROPHOSPHATE; TITANIUM DIOXIDE; METHYLPARABEN; POLYETHYLENE GLYCOL 400; PROPYLPARABEN; CALCIUM CARBONATE

4872 Morning Fresh Toothpaste NDC 67777-175-01
4873 Morning Fresh Toothpaste NDC 67777-175-02

Active Ingredient

Sodium Monofluorophosphate 0.76 %

Purpose

Anticavity

Use(s)

- Helps protect against cavities

Warnings

• Do not swallow

Keep out of reach of children under 6 years of age

If you accidentally swallow more than used for brushing, get medical help or contact a Poison Control Center (1-800-222-1222) immediately.

Directions

• Adults and children 2 years and older: Brush teeth thoroughly after meals or at least twice a day or use as directed by a dentist or physician.

• Children under 6 years: To minimize swallowing, use a pea sized amount and supervise brushing and rinsing until good habits are established.

• Children under 2 years: Use as Directed by a dentist or physician.

Inactive Ingredient

Calcium Carbonate, Carboxymethylcellulose Sodium, Flavor, Methylparaben, Polyethyene Glycol 400, Propylparaben, Saccharin Sodium, Silicon Sioxide, Sodium Benzoate, Sodium Lauryl Sulphate, Sodium Pyrophosphate, Sodium Silicate, Sorbitol, Titanium Dioxide, Water

Other Information

Store between 15º - 35ºC (59º - 95ºF)

Questions?

1-888-396-2739 Monday - Friday 9AM - 5PM EST

Label

4872 Morning Fresh Toothpaste, with Fluoride

Label

4873 Morning Fresh Toothpaste, With Fluoride